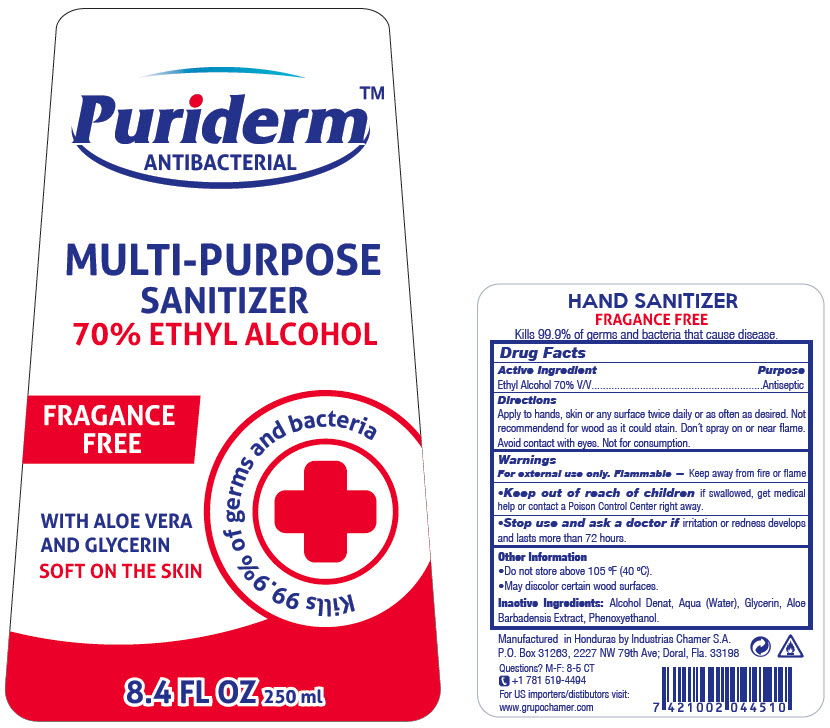 DRUG LABEL: PURIDERM 
NDC: 51774-005 | Form: LIQUID
Manufacturer: INDUSTRIAS CHAMER S.A. DE C.V.
Category: otc | Type: HUMAN OTC DRUG LABEL
Date: 20200825

ACTIVE INGREDIENTS: ALCOHOL 70 mL/100 mL
INACTIVE INGREDIENTS: WATER; GLYCERIN; ALOE VERA LEAF; PHENOXYETHANOL

PURIDERM™ ANTIBACTERIAL

Drug Facts

Active Ingredient

Ethyl Alcohol 70% V/V

Purpose

Antiseptic

Directions

INDICATIONS AND USAGE

Apply to hands, skin or any surface twice daily or as often as desired. Not recommendend for wood as it could stain. Don´t spray on or near flame. Avoid contact with eyes. Not for consumption.

Warnings

For external use only. Flammable — Keep away from fire or flame

- Keep out of reach of children if swallowed, get medical help or contact a Poison Control Center right away.

- Stop use and ask a doctor if irritation or redness develops and lasts more than 72 hours.

Other Information

- Do not store above 105 °F (40 °C).
- May discolor certain wood surfaces.

Inactive Ingredients

Alcohol Denat, Aqua (Water), Glycerin, Aloe Barbadensis Extract, Phenoxyethanol.

Questions?

M-F: 8-5 CT
+1 781 519-4494

PRINCIPAL DISPLAY PANEL - 250 ml Bottle Label

Puriderm™
ANTIBACTERIAL

MULTI-PURPOSE
SANITIZER
70% ETHYL ALCOHOL

FRAGANCE
FREE

Kills 99.9% of germs and bacteria

WITH ALOE VERA
AND GLYCERIN

SOFT ON THE SKIN

8.4 FL OZ 250 ml